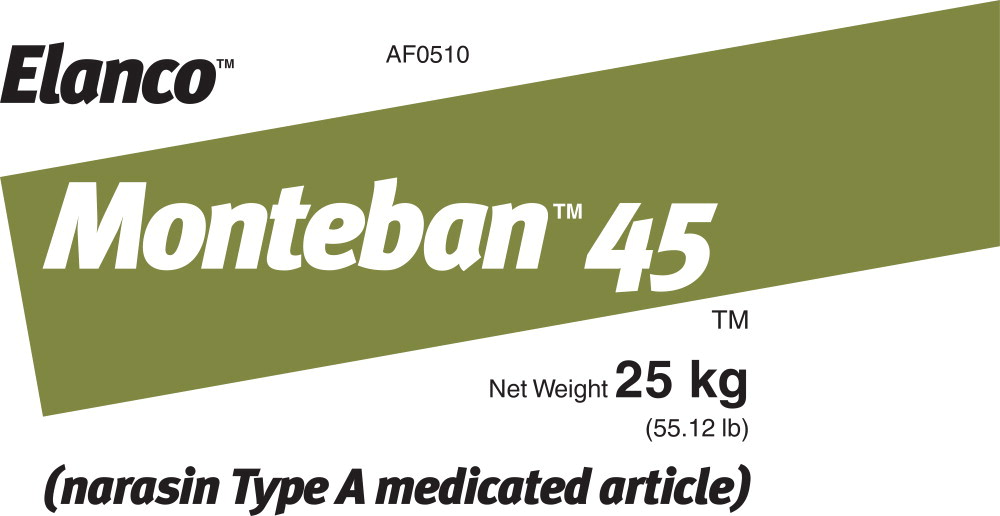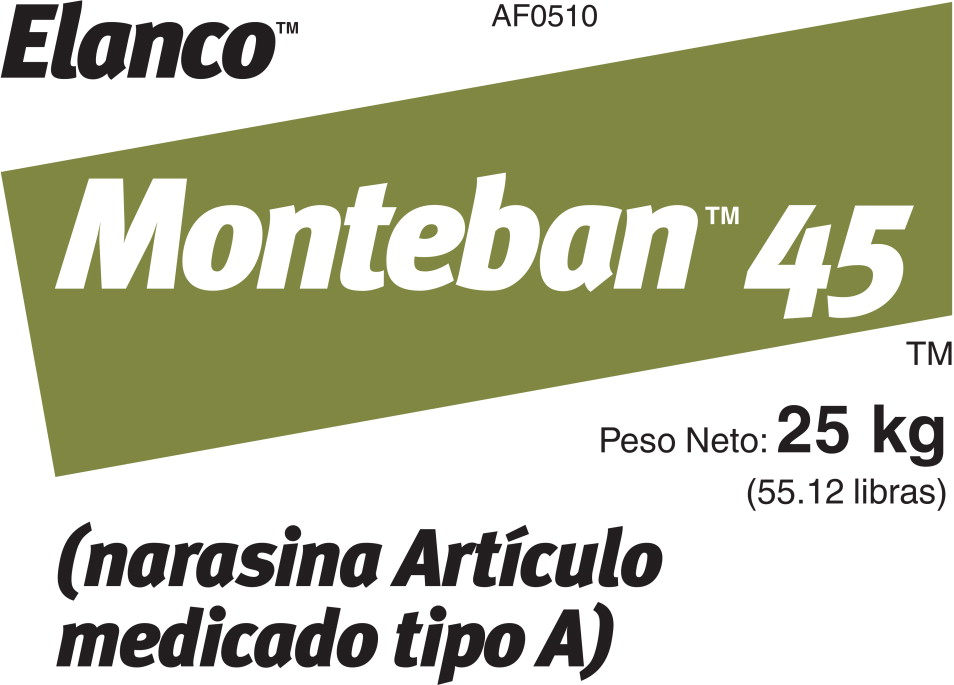 DRUG LABEL: Monteban 45
NDC: 58198-0510 | Form: GRANULE
Manufacturer: Elanco US Inc.
Category: animal | Type: OTC TYPE A MEDICATED ARTICLE ANIMAL DRUG LABEL
Date: 20240605

ACTIVE INGREDIENTS: narasin 100 g/1 kg

Elanco™
Monteban™45TM

Net Weight 25 kg
(55.12 lb)

(narasin Type A medicated article)

For Use in Broiler Chicken Feeds Only

Do Not Feed Undiluted.

Active Drug Ingredient: narasin ........................................................... 45 g per lb

For the prevention of coccidiosis caused by Eimeria necatrix, E. tenella, E. acervulina, E. brunetti, E. mivati, and E. maxima.

Important: Must be thoroughly mixed in feeds before use.

Mixing Directions:

Type C Feeds - Amounts of Monteban 45 necessary to manufacture one ton of Type C medicated feed containing 54 to 90 g narasin are shown in the table. A preblend of Monteban in 15 - 20 lbs of feed should be made before incorporating into the total amount of finished Type C medicated feed.

The drug concentration should be adjusted to meet the severity of the coccidial challenge, which varies with environmental and management conditions.

Narasin Type C Concentration (Grams/Ton) | Monteban (Lbs/Ton of Type C Feed)
 | Lbs
54 | 1.20
59 | 1.31
63 | 1.40
68 | 1.51
72 | 1.60
81 | 1.80
90 | 2.00

Type B Feeds - Amounts of Monteban 45 necessary to manufacture one ton of Type B medicated feed containing up to 5,400 g narasin are shown in the table.

Narasin Type B Concentration (Grams/Ton) | Monteban (Lbs/Ton of Type B feed)
1 ,350 2,700 5,400 | 30 60 120

Feeding Directions — Feed the resulting Type C medicated feed continuously as the sole ration.

CAUTION: Do not allow adult turkeys, horses or other equines access to narasin formulations. Ingestion of narasin by these species has been fatal

NOT FOR HUMAN USE

WARNINGS

WARNING: When mixing and handling Monteban, use protective clothing, impervious gloves and a dust mask. Operators should wash thoroughly with soap and water after handling. If accidental eye contact occurs, immediately rinse thoroughly with water.

Store at or below 25° C (77° F). Excursions permitted to 37° C (99° F).
Not to be used after the date printed at top of bag.

PRINTED WITH SOY INK™

TAKE TIME

OBSERVE LABEL
DIRECTIONS

Monteban, Elanco and the diagonal bar logo are trademarks of Elanco or its affiliates.

Restricted Drug (California) - Use Only as Directed
Approved by FDA under NADA # 118-980
Elanco US Inc.
Greenfield, IN 46140, USA

To report adverse effects, access medical information, or obtain additional product information, call 1-800-428-4441.

BG102243X

Elanco™ Monteban™45TM

Peso Neto: 25 kg
(55.12 libras)

(narasina Artículo medicado tipo A)

Solo para uso en alimento para pollos de engorde
No administrar sin diluir

Principio activo: narasina ........................................................... 100 g/kg (45 g/lb)

Para la prevención de la coccidiosis causada por Eimeria necatrix, E. tenella, E. acervulina, E. brunetti, E. mivati y E. maxima.

Importante: Debe mezclarse bien con el alimento antes de usar.

Instrucciones de mezclado:

Alimentos tipo C: En la tabla se muestran las cantidades de Monteban 45 necesarias para elaborar una tonelada corta de alimento tipo C medicado que contenga de 54 a 90 g de narasina. Se recomienda hacer una premezcla de Monteban en 7 a 10 kg (15 a 20 lb) de alimento antes de incorporarla a la cantidad total del alimento medicado tipo C terminado. La concentración del fármaco debe ajustarse de acuerdo con la gravedad de la infestación coccidial, que varÍa con las condiciones medioambientales y de manejo.

Narasina en concentración para alimentos tipo C (g/ton corta) | Monteban (lb/ton corta de alimento tipo C) | Narasina (g/ton métrica) | Monteban (kg/ton métrica)
g 54 59 63 68 72 81 90 | lb 1.20 1 .31 1 .40 1 .51 1.60 1.80 2.00 | g 60 65 70 75 80 90 100 | kg 0.600 0.650 0.700 0.750 0.800 0.900 1.000

Alimentos tipo B: En la tabla se muestran las cantidades de Monteban 45 necesarias para elaborar una tonelada corta de alimento medicado tipo B con un contenido de hasta 5,400 g de narasina.

Narasina en concentración para alimentos tipo B (g/ton corta) | Monteban (lb/ton corta de alimento tipo B) | Narasina (g/ton métrica) | Monteban (kg/ton métrica)
1 ,350 2,700 5,400 | 30 60 120 | 1 ,500 3,000 6,000 | 15.0 30.0 60.0

Instrucciones de administración: Administrar el alimento medicado tipo C resultante de manera continua como la única ración.

PRECAUCIÓN: No permita que pavos adultos, caballos u otros equinos tengan acceso a formulaciones con narasina. La ingestión de narasina por estas especies ha sido mortal.

NO USAR EN SERES HUMANOS

WARNINGS

ADVERTENCIA: Cuando se mezcle o manipule Monteban use ropa protectora, guantes impermeables y mascarilla contra polvo. Los operarios deben lavarse bien con agua y jabón tras manipular el producto. Si ocurre contacto accidental con los ojos, se deberán enjuagar inmediatamente con agua abundante.

Conservar a una temperatura igual o menor a 25 ° C (77 ° F). Se permiten variaciones hasta 37 ° C (99 ° F). No se deberá usar después de la fecha impresa en la parte superior del saco.

Monteban, Elanco y el logo de la barra diagonal son marcas de Elanco o sus afiliadas.

Medicamento Restringido (California) - Usar solo según las indicaciones Aprobado por la FDA bajo NADA # 118-980
Elanco US Inc.
Greenfield, IN 46140,
Estados Unidos de América

Para notificar de efectos adversos, tener acceso a información médica u obtener información adicional sobre el producto, llame al 1-800-428-4441.

BG102243X

Principal Display Panel - Monteban 45 Label

Elanco™

Monteban™45™

Net Weight 25 kg
(55.12 lb)

(narasin Type A medicated article)

PACKAGE LABEL

Elanco™

Monteban™45™

Peso Neto: 25 kg
(55.12 libras)

(narasina Artículo medicado tipo A)